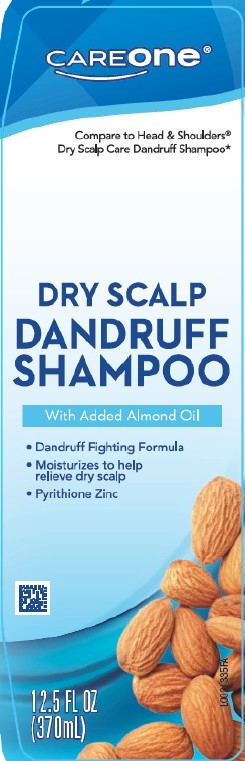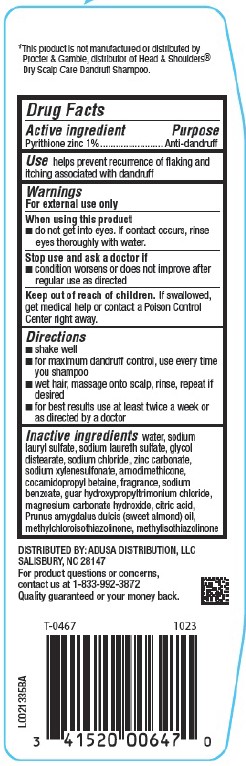 DRUG LABEL: Dry Scalp Dandruff
NDC: 72476-281 | Form: SHAMPOO
Manufacturer: Retail Business Services, LLC 
Category: otc | Type: HUMAN OTC DRUG LABEL
Date: 20260206

ACTIVE INGREDIENTS: PYRITHIONE ZINC 10 mg/1 mL
INACTIVE INGREDIENTS: SODIUM LAURYL SULFATE; SODIUM LAURETH SULFATE; GLYCOL DISTEARATE; SODIUM CHLORIDE; WATER; ZINC CARBONATE; SODIUM XYLENESULFONATE; AMODIMETHICONE (800 CST); COCAMIDOPROPYL BETAINE; SODIUM BENZOATE; GUAR HYDROXYPROPYLTRIMONIUM CHLORIDE (1.7 SUBSTITUENTS PER SACCHARIDE); MAGNESIUM CARBONATE HYDROXIDE; CITRIC ACID MONOHYDRATE; ALMOND OIL; METHYLCHLOROISOTHIAZOLINONE; METHYLISOTHIAZOLINONE

Care One 281.007/281AK,AN
Dandruff Shampoo, Dry Scalp

Disclaimer

*This product is not manufactured or distributed by Procter & Gamble, distributor of Head & Shoulders® Dry Scalp Care Dandruff Shampoo.

Active ingredient

Pyrithione zinc 1%

Purpose

Anti-dandruff

Use

helps prevent recurrence of flaking and itching associated with dandruff

Warnings

For external use only

When using this product

- do not get into eyes. If contact occurs, rinse eyes thoroughly with water.

Stop use and ask a doctor if

- condition worsens or does not improve after regular use as directed

Keep out of reach of children.

If swallowed, get medical help or contact a Poison Control Center right away.

Directions

- shake well
- for maximum dandruff control, use everytime you shampoo
- wet hair, massage onto scalp, rinse, repeat if desired
- for best results use at least twice a week or as directed by a doctor

inactive ingredients

water, sodium lauryl sulfate, sodium laureth sulfate, glycol distearate, sodium chloride, zinc carbonate, sodium xylenesulfonate, amodimethicone, cocamidopropyl betaine, fragrance, sodium benzoate, guar hydroxypropyltrimonium chloride, magnesium carbonate hydroxide, citric acid, Prunus amygdalus dulcis (sweet almond) oil, methylchloroisothiazolinone, methylisothiazolinone

Adverse reaction

DISTRIBUTED BY: ADUSA DISTRIBUTION, LLC

SALISBURY, NC 28147

For product questions or concerns, contact us at 1-833-992-3872

Quality guaranteed or your money back.

Principal Display Panel

CAREone®

Compare to Head & Shoulders®Dry Scalp Care Dandruff Shampoo*

DRY SCALP DANDRUFF SHAMPOO

With Added Almond Oil

- Dandruff Fighting Formula
- Moisturizes to help relieve dry scalp
- Pyrithione Zinc

12.5 FL OZ (370 mL)